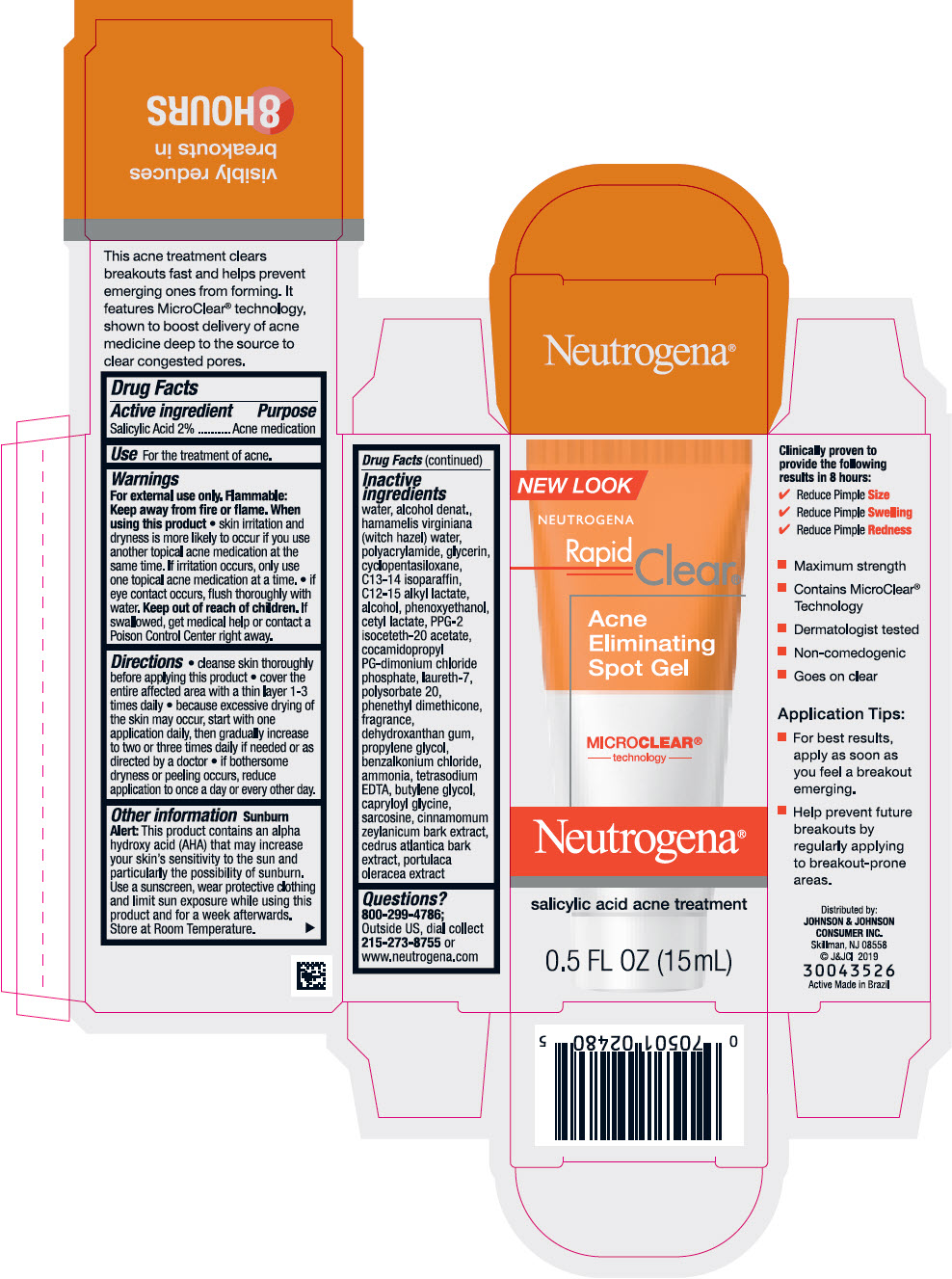 DRUG LABEL: Neutrogena Rapid Clear Acne Eliminating Spot
NDC: 69968-0472 | Form: GEL
Manufacturer: Kenvue Brands LLC
Category: otc | Type: HUMAN OTC DRUG LABEL
Date: 20241111

ACTIVE INGREDIENTS: SALICYLIC ACID 20 mg/1 mL
INACTIVE INGREDIENTS: BUTYLENE GLYCOL; CAPRYLOYL GLYCINE; SARCOSINE; CINNAMON BARK OIL; CEDRUS ATLANTICA BARK; PURSLANE; WATER; HAMAMELIS VIRGINIANA TOP WATER; GLYCERIN; CYCLOMETHICONE 5; C13-14 ISOPARAFFIN; C12-15 ALKYL LACTATE; ALCOHOL; PHENOXYETHANOL; CETYL LACTATE; PPG-2 ISOCETETH-20 ACETATE; COCAMIDOPROPYL PROPYLENE GLYCOL-DIMONIUM CHLORIDE PHOSPHATE; LAURETH-7; POLYSORBATE 20; DEHYDROXANTHAN GUM; PROPYLENE GLYCOL; BENZALKONIUM CHLORIDE; AMMONIA; EDETATE SODIUM

Neutrogena® Rapid Clear® Acne Eliminating Spot Gel

Drug Facts

Active ingredient

Salicylic Acid 2%

Purpose

Acne Medication

Use

For the treatment of acne.

Warnings

For external use only.

Flammable

Keep away from fire or flame.

When using this product

- skin irritation and dryness is more likely to occour if you use another tropical acne medication at the same time. If irritation occurs, only use one topical medication at a time

KEEP OUT OF REACH OF CHILDREN

- if eye contact occurs, flush thoroughly with water. Keep out of reach of children. If swallowed, get medical help or contact a Poison Control Center right away.

Directions

- cleanse the skin thoroughly before applying product.
- cover the entire affected area with a thin layer 1-3 times daily.
- because excessive drying of the skin may occur, start with one application daily, then gradually increase to two or three times daily if needed or as directed by a doctor.
- if bothersome dryness or peeling occurs, reduce application to every other day.

Other information

Sunburn Alert

This product contains an alpha hydroxy acid (AHA) that may increase your skin's sensitivity to the sun and particularly the possibility of sunburn. Use a sunscreen, wear a protective clothing, and limit sun exposure while using this product and for a week afterwards. Store at Room Temperature.

Inactive ingredients

water, alcohol denat., hamamelis virginiana (witch hazel) water, polyacrylamide, glycerin, cyclopentasiloxane, C13-14 isoparaffin, C12-15 alkyl lactate, alcohol, phenoxyethanol, cetyl lactate, PPG-2 isoceteth-20 acetate, cocamidopropyl PG-dimonium chloride phosphate, laureth-7, polysorbate 20, phenethyl dimethicone, fragrance, dehydroxanthan gum, propylene glycol, benzalkonium chloride, ammonia, tetrasodium EDTA, butylene glycol, capryloyl glycine, sarcosine, cinnamomum zeylanicum bark extract, cedrus atlantica bark extract, portulaca oleracea extract

Questions?

800-299-4786; Outside US dial collect US , 215-273-8755 or www.neutrogena.com

Distributed by:
JOHNSON & JOHNSON
CONSUMER INC.
Skillman, NJ 08558

PRINCIPAL DISPLAY PANEL - 15 mL Tube Carton

NEW LOOK

NEUTROGENA
Rapid
Clear®

Acne
Eliminating
Spot Gel

MICRO CLEAR®
technology

Neutrogena®

salicylic acid acne treatment

0.5 FL OZ (15mL)